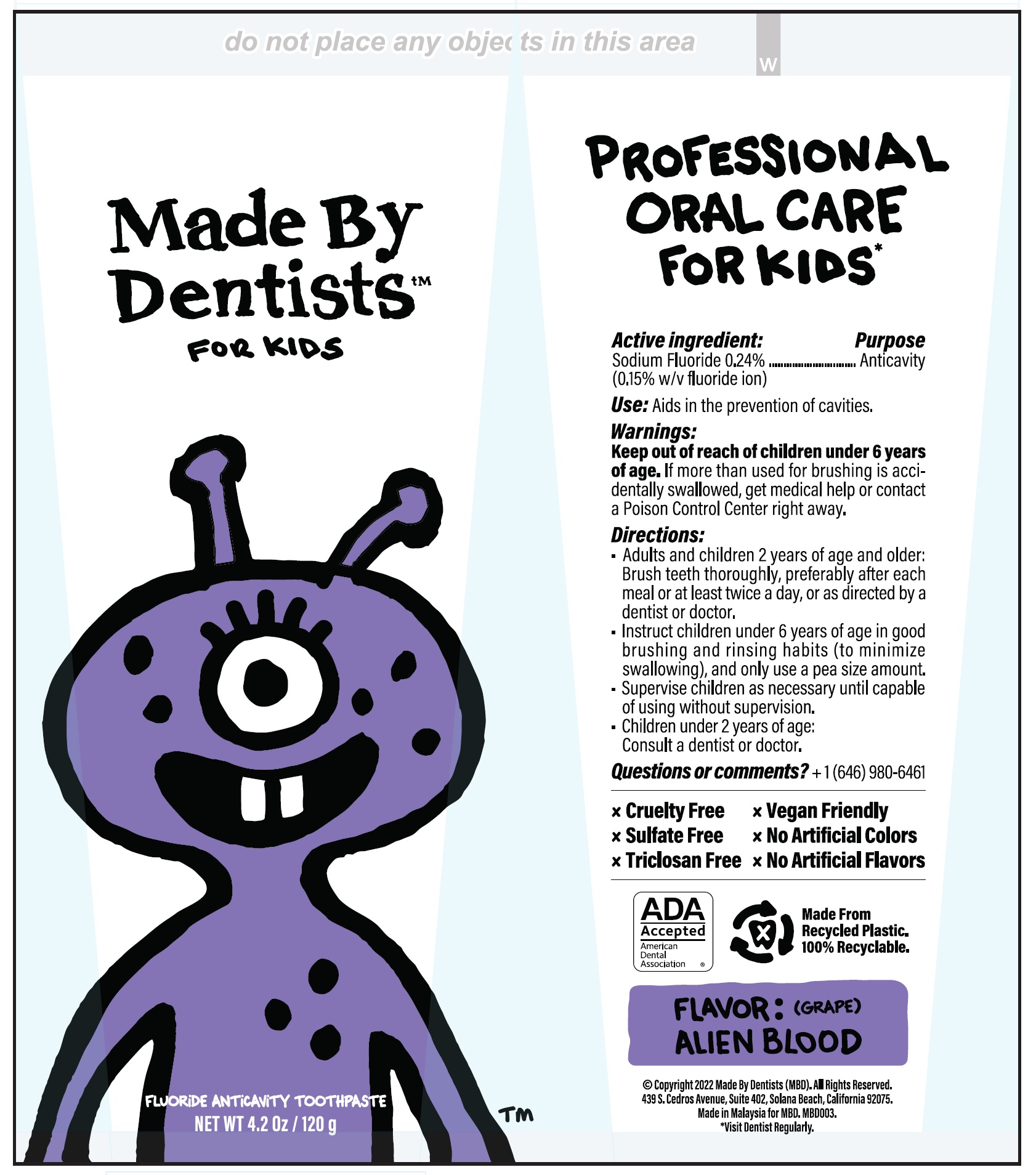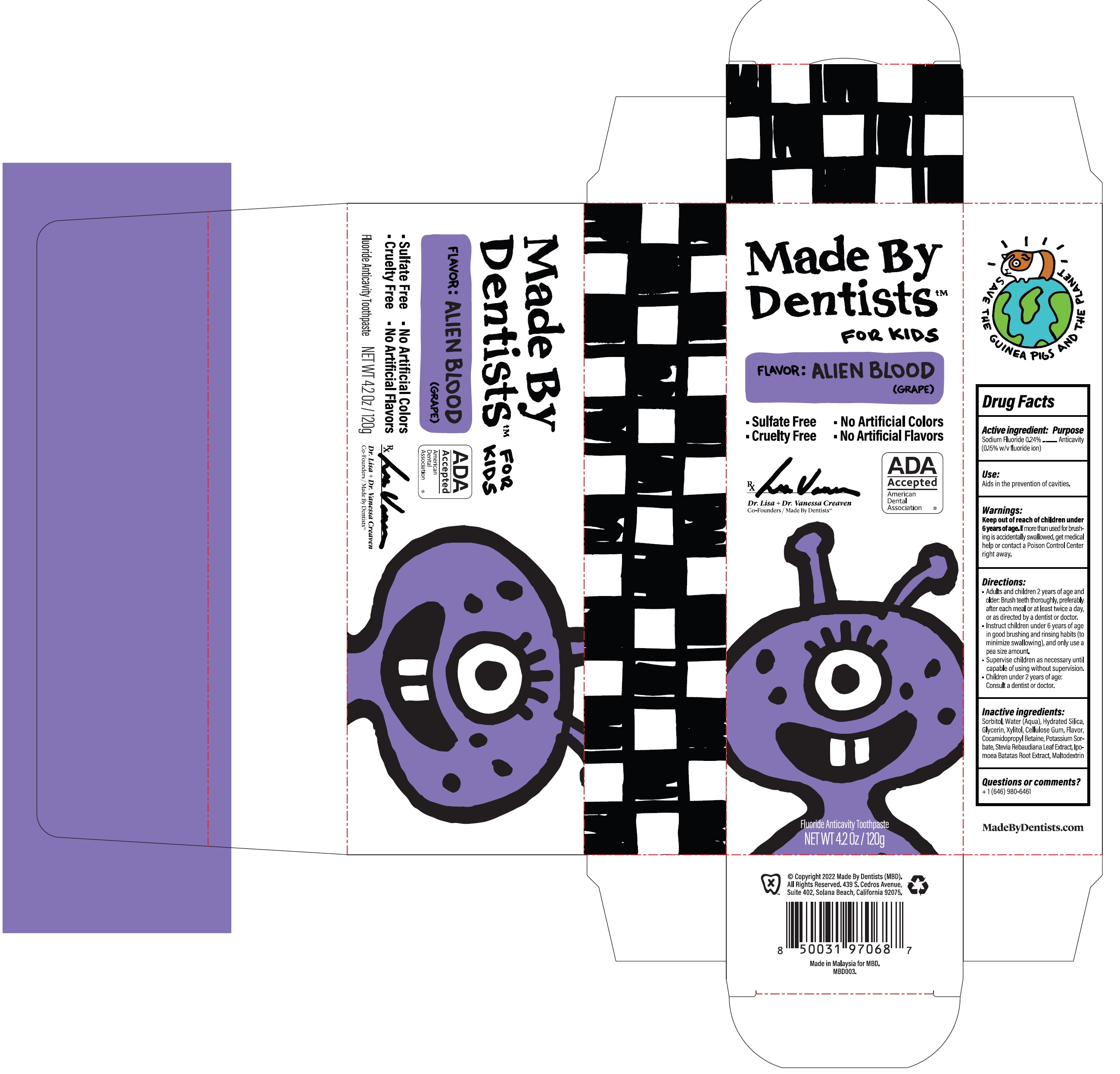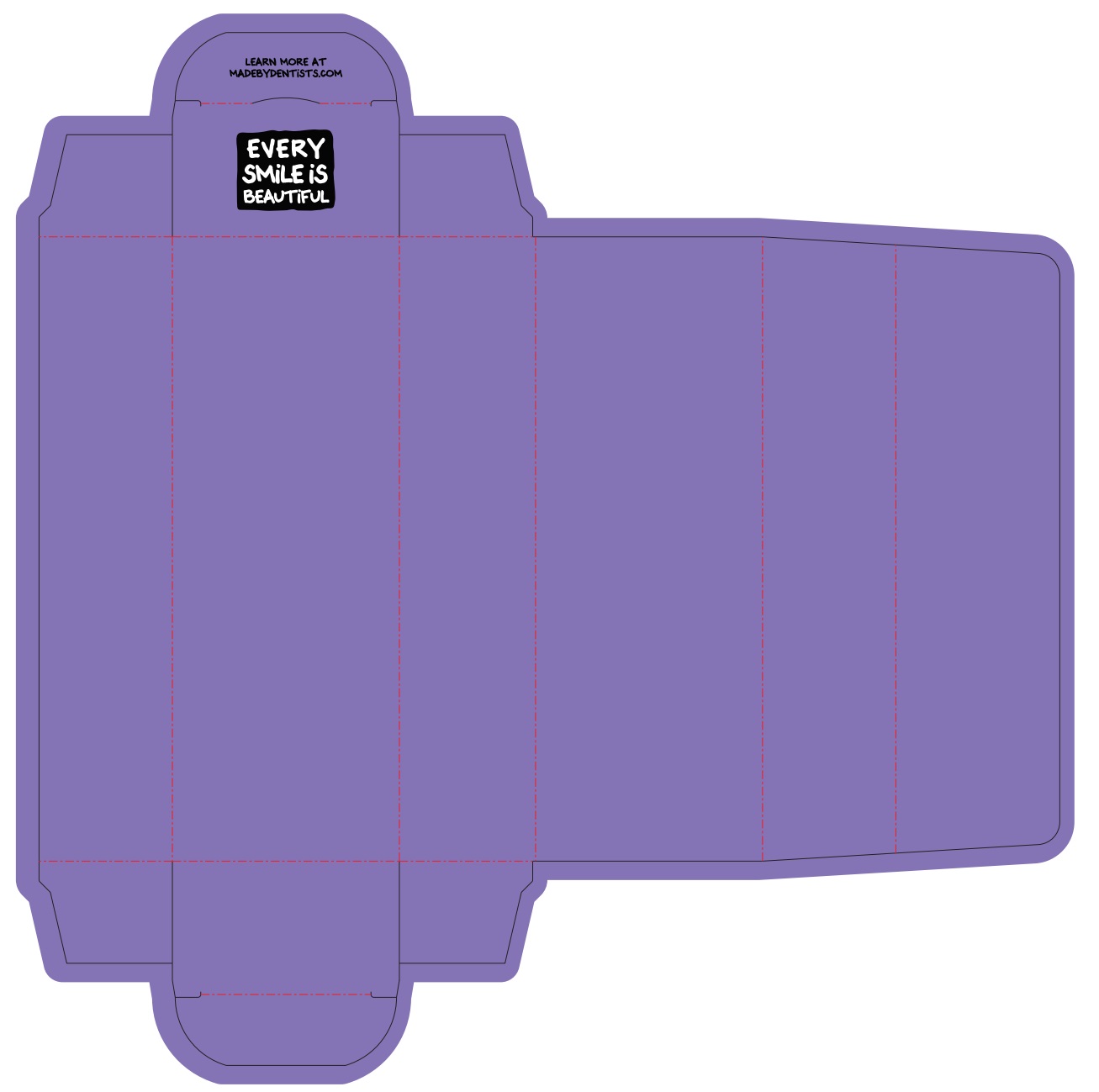 DRUG LABEL: Made by Dentists For Kids Alien Blood
NDC: 75065-026 | Form: PASTE
Manufacturer: MADE BY DENTISTS INC
Category: otc | Type: HUMAN OTC DRUG LABEL
Date: 20251208

ACTIVE INGREDIENTS: SODIUM FLUORIDE 1.5 mg/1 g
INACTIVE INGREDIENTS: SORBITOL; WATER; HYDRATED SILICA; GLYCERIN; XYLITOL; CARBOXYMETHYLCELLULOSE SODIUM, UNSPECIFIED; COCAMIDOPROPYL BETAINE; POTASSIUM SORBATE; STEVIA REBAUDIUNA LEAF; SWEET POTATO; MALTODEXTRIN

Made by Dentists For Kids Alien Blood

Active ingredient:

Sodium Fluoride 0.24% (0.15% w/v fluoride ion)

Purpose

Anticavity

Use:

Aids in the prevention of cavities.

Warnings:

Keep out of reach of children under 6 years of age.

If more than used for brushing is accidentlly swallowed, get medical help or contact a Poison Control Center right away.

Directions:

- Adults and children 2 years of age and older: Brush teeth thoroughly, preferably after each meal or at least twice a day, or as directed by a dentist or doctor.
- Instruct children under 6 years of age in good brushing and rinsing habits (to minimize swallowing), and only use a pea size amount.
- Supervise children as necessary until capable of using without supervision.
- Children under 2 years of age: Consult a dentist or doctor.

Inactive ingredients:

Sorbitol, Water (Aqua), Hydrated Silica, Glycerin, Xylitol, Cellulose Gum, Flavor, Cocamidopropyl Betaine, Potassium Sorbate, Stevia Rebaudiana Leaf Extract, Ipomoea Batatas Root Extract, Maltodextrin

Questions or comments?

+ 1 (646) 980-6461